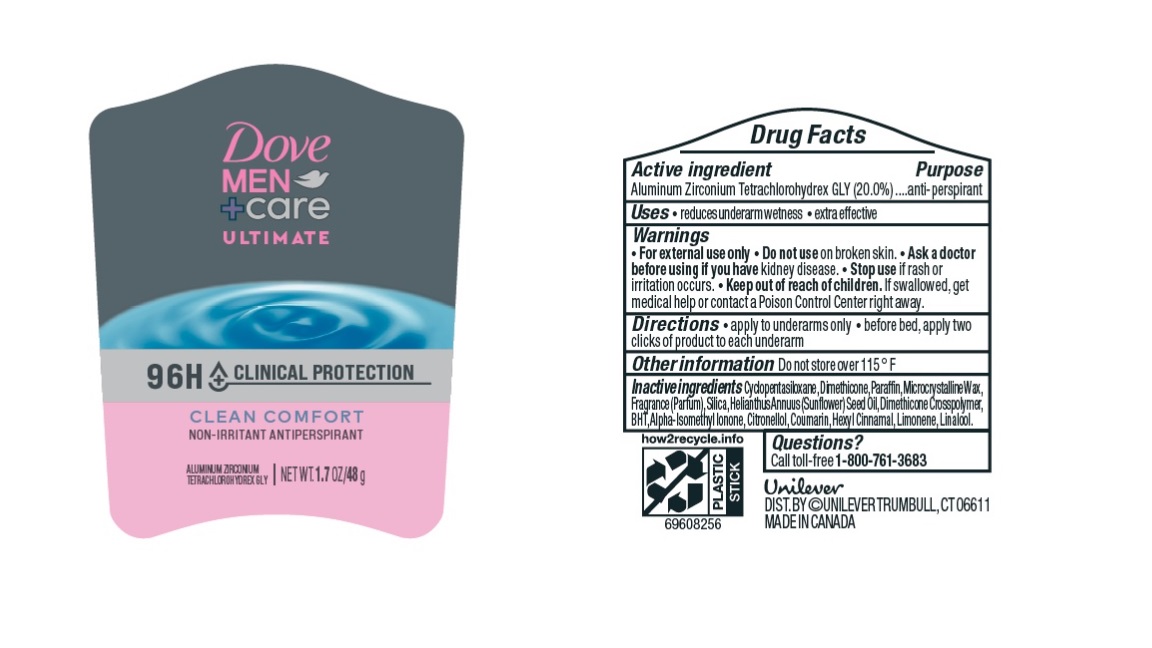 DRUG LABEL: Dove
NDC: 64942-2120 | Form: STICK
Manufacturer: Conopco Inc. d/b/a/ Unilever
Category: otc | Type: HUMAN OTC DRUG LABEL
Date: 20241024

ACTIVE INGREDIENTS: ALUMINUM ZIRCONIUM TETRACHLOROHYDREX GLY 20 g/100 g
INACTIVE INGREDIENTS: LINALOOL, (+/-)-; .ALPHA.-HEXYLCINNAMALDEHYDE; ISOMETHYL-.ALPHA.-IONONE; .BETA.-CITRONELLOL, (R)-; COUMARIN; MICROCRYSTALLINE WAX; PARAFFIN; SUNFLOWER OIL; CYCLOMETHICONE 5; BUTYLATED HYDROXYTOLUENE; SILICON DIOXIDE; DIMETHICONE; DIMETHICONE CROSSPOLYMER (450000 MPA.S AT 12% IN CYCLOPENTASILOXANE); LIMONENE, (+)-

Dove Men + Care 96H Clinical Protection Clean Comfort Antiperspirant

Drug Facts

Active ingredient

Aluminum Zirconium Tetrachlorohydrex GLY (20.0 %)

Purpose

antiperspirant

Uses

• reduces underarm wetness
• extra effective

Warnings

• For external use only.
• Do not use on broken skin .
• Ask a doctor before use if you have kidney disease.
• Stop use if rash or irritation occurs.

• Keep out of reach of children.

If swallowed, get medical help or contact a Poison Control Center right away.

Directions

• apply to underarms only
• before bed, apply two clicks of product to each underarm

Other information

Do not store over 115°F

Inactive ingredients

Cyclopentasiloxane, Dimethicone, Paraffin, Microcrystalline Wax, Fragrance (Parfum), Silica, Helianthus Annuus (Sunflower) Seed Oil, Dimethicone Crosspolymer, BHT, Alpha-Isomethyl Ionone, Citronellol, Coumarin, Hexyl Cinnamal, Limonene, Linalool

Questions?

Call toll-free 1-800-761-3683